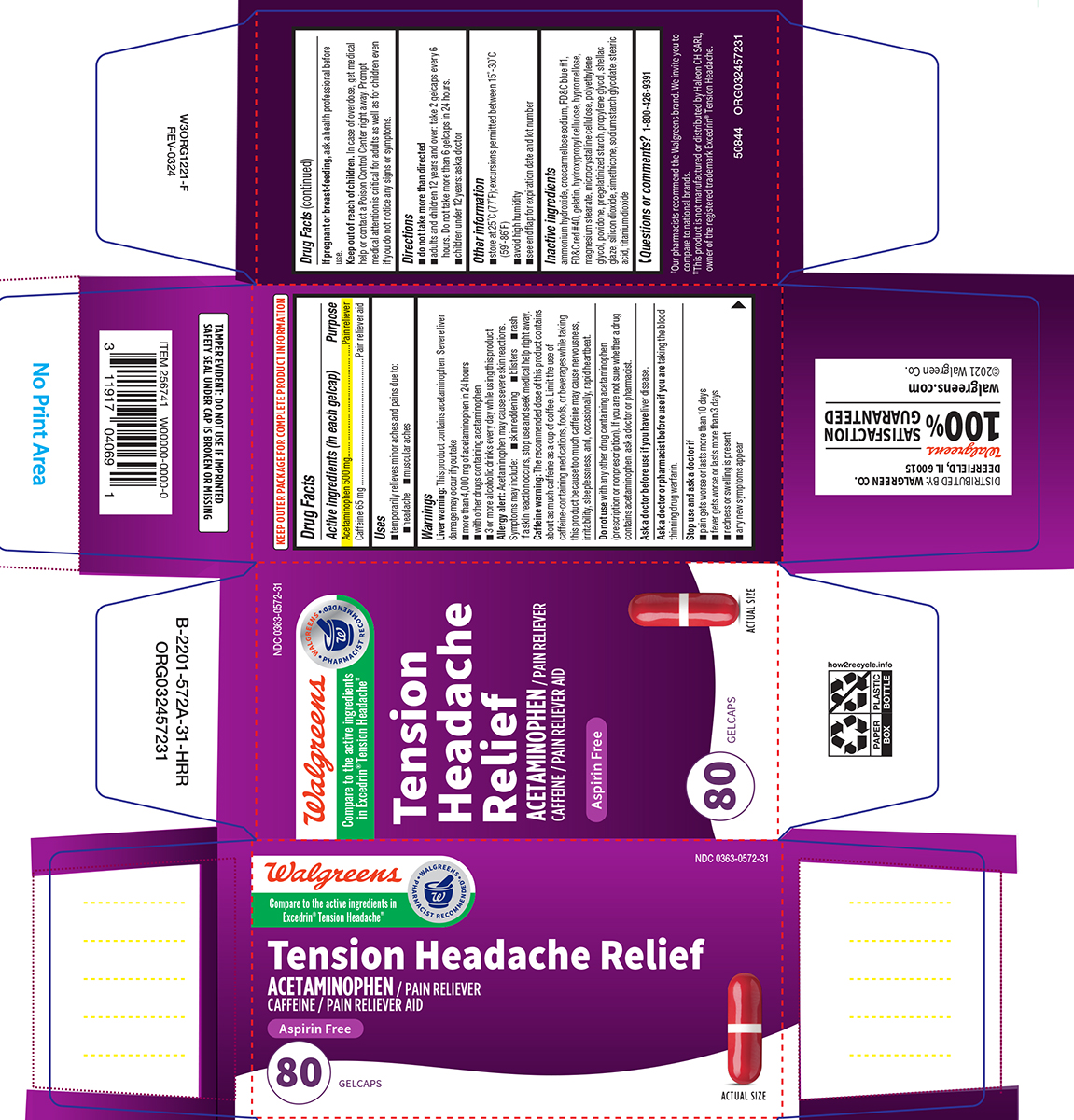 DRUG LABEL: Tension Headache Relief
NDC: 0363-0572 | Form: TABLET, COATED
Manufacturer: Walgreen Company
Category: otc | Type: HUMAN OTC DRUG LABEL
Date: 20250709

ACTIVE INGREDIENTS: ACETAMINOPHEN 500 mg/1 1; CAFFEINE 65 mg/1 1
INACTIVE INGREDIENTS: AMMONIA; CROSCARMELLOSE SODIUM; FD&C BLUE NO. 1; FD&C RED NO. 40; GELATIN, UNSPECIFIED; HYDROXYPROPYL CELLULOSE, UNSPECIFIED; HYPROMELLOSE, UNSPECIFIED; MAGNESIUM STEARATE; MICROCRYSTALLINE CELLULOSE; POLYETHYLENE GLYCOL, UNSPECIFIED; POVIDONE, UNSPECIFIED; STARCH, CORN; PROPYLENE GLYCOL; SHELLAC; SILICON DIOXIDE; SODIUM STARCH GLYCOLATE TYPE A POTATO; STEARIC ACID; TITANIUM DIOXIDE

Walgreens 44-572

Active ingredients (in each gelcap)

Acetaminophen 500 mg
Caffeine 65 mg

Purpose

Pain reliever
Pain reliever aid

Uses

- temporarily relieves minor aches and pains due to:
  - headache
  - muscular aches

Warnings

Liver warning: This product contains acetaminophen. Severe liver damage may occur if you take

- more than 4,000 mg of acetaminophen in 24 hours
- with other drugs containing acetaminophen
- 3 or more alcoholic drinks every day while using this product

Allergy alert: Acetaminophen may cause severe skin reactions. Symptoms may include:

- skin reddening
- blisters
- rash

If a skin reaction occurs, stop use and seek medical help right away.

Caffeine warning: The recommended dose of this product contains about as much caffeine as a cup of coffee. Limit the use of caffeine-containing medications, foods, or beverages while taking this product because too much caffeine may cause nervousness, irritability, sleeplessness, and, occasionally, rapid heartbeat.

Do not use

with any other drug containing acetaminophen (prescription or nonprescription). If you are not sure whether a drug contains acetaminophen, ask a doctor or pharmacist.

Ask a doctor before use if you have

liver disease.

Ask a doctor or pharmacist before use if you are

taking the blood thinning drug warfarin.

Stop use and ask a doctor if

- pain gets worse or lasts more than 10 days
- fever gets worse or lasts more than 3 days
- redness or swelling is present
- any new symptoms appear

If pregnant or breast-feeding,

ask a health professional before use.

Keep out of reach of children.

In case of overdose, get medical help or contact a Poison Control Center right away. Prompt medical attention is critical for adults as well as for children even if you do not notice any signs or symptoms.

Directions

- do not take more than directed
- adults and children 12 years and over: take 2 gelcaps every 6 hours. Do not take more than 6 gelcaps in 24 hours.
- children under 12 years: ask a doctor

Other information

- store at 25ºC (77ºF); excursions permitted between 15º-30ºC (59º-86ºF)
- avoid high humidity
- see end flap for expiration date and lot number

Inactive ingredients

ammonium hydroxide, croscarmellose sodium, FD&C blue #1, FD&C red #40, gelatin, hydroxypropyl cellulose, hypromellose, magnesium stearate, microcrystalline cellulose, polyethylene glycol, povidone, pregelatinized starch, propylene glycol, shellac glaze, silicon dioxide, simethicone, sodium starch glycolate, stearic acid, titanium dioxide

Questions or comments?

1-800-426-9391

Principal Display Panel

Walgreens

Compare to the active ingredients
in Excedrin® Tension Headache††

• WALGREENS •
PHARMACIST RECOMMENDED†

NDC 0363-0572-31

Tension
Headache
Relief

ACETAMINOPHEN / PAIN RELIEVER
CAFFEINE / PAIN RELIEVER AID

ASPIRIN FREE

80 GELCAPS

ACTUAL SIZE

TAMPER EVIDENT: DO NOT USE IF IMPRINTED
SAFETY SEAL UNDER CAP IS BROKEN OR MISSING

†Our pharmacists recommend the Walgreens brand. We invite you
to compare to national brands.

††This product is not manufactured or distributed by Haleon CH SARL,
owner of the registered trademark Excedrin® Tension Headache

DISTRIBUTED BY: WALGREEN CO.
DEERFIELD, IL 60015
Walgreens
100% SATISFACTION
GUARANTEED
walgreens.com ©2021 Walgreen Co.

50844 ORG032457231

Walgreens 44-572